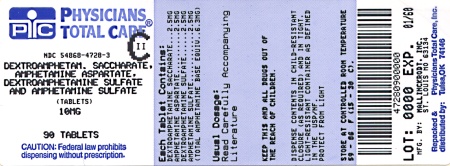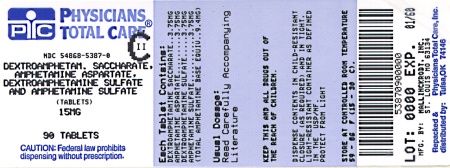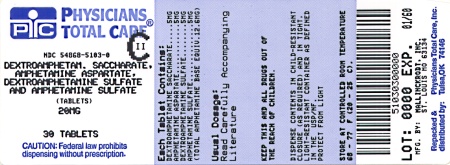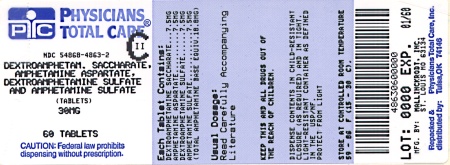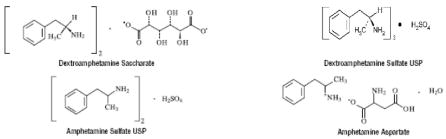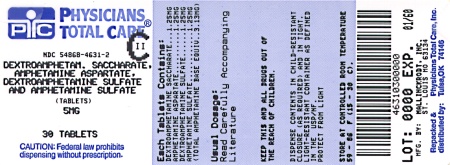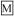 DRUG LABEL: Dextroamphetamine saccharate, amphetamine aspartate monohydrate, dextroamphetamine sulfate and amphetamine sulfate
NDC: 54868-4631 | Form: TABLET
Manufacturer: Physicians Total Care, Inc.
Category: prescription | Type: HUMAN PRESCRIPTION DRUG LABEL
Date: 20130709
DEA Schedule: CII

ACTIVE INGREDIENTS: DEXTROAMPHETAMINE SACCHARATE 1.25 mg/1 1; AMPHETAMINE ASPARTATE 1.25 mg/1 1; DEXTROAMPHETAMINE SULFATE 1.25 mg/1 1; AMPHETAMINE SULFATE 1.25 mg/1 1
INACTIVE INGREDIENTS: CELLULOSE, MICROCRYSTALLINE; SILICON DIOXIDE; POVIDONE; STEARIC ACID

CII Rx Only

BOXED WARNING

AMPHETAMINES HAVE A HIGH POTENTIAL FOR ABUSE. ADMINISTRATION OF AMPHETAMINES FOR PROLONGED PERIODS OF TIME MAY LEAD TO DRUG DEPENDENCE AND MUST BE AVOIDED. PARTICULAR ATTENTION SHOULD BE PAID TO THE POSSIBILITY OF SUBJECTS OBTAINING AMPHETAMINES FOR NON-THERAPEUTIC USE OR DISTRIBUTION TO OTHERS, AND THE DRUGS SHOULD BE PRESCRIBED OR DISPENSED SPARINGLY.

MISUSE OF AMPHETAMINE MAY CAUSE SUDDEN DEATH AND SERIOUS CARDIOVASCULAR ADVERSE EVENTS.

DESCRIPTION

A single-entity amphetamine product combining the neutral sulfate salts of dextroamphetamine and amphetamine, with the dextro isomer of amphetamine saccharate and d, I-amphetamine aspartate. The structural formulas are as follows:

Each Tablet Contains:
 | 5 mg | 7.5 mg | 10 mg | 12.5 mg | 15 mg | 20 mg | 30 mg
Dextroamphetamine Saccharate | 1.25 mg | 1.875 mg | 2.5 mg | 3.125 mg | 3.75 mg | 5 mg | 7.5 mg
Amphetamine Aspartate | 1.25 mg | 1.875 mg | 2.5 mg | 3.125 mg | 3.75 mg | 5 mg | 7.5 mg
Dextroamphetamine Sulfate USP | 1.25 mg | 1.875 mg | 2.5 mg | 3.125 mg | 3.75 mg | 5 mg | 7.5 mg
Amphetamine Sulfate USP | 1.25 mg | 1.875 mg | 2.5 mg | 3.125 mg | 3.75 mg | 5 mg | 7.5 mg
Total amphetamine base equivalence | 3.13 mg | 4.75 mg | 6.3 mg | 7.8 mg | 9.4 mg | 12.6 mg | 18.8 mg

In addition, each tablet contains the following inactive ingredients: Microcrystalline Cellulose NF, Silicon Dioxide NF, Povidone USP, and Stearic Acid NF.

CLINICAL PHARMACOLOGY

Pharmacodynamics

Amphetamines are non-catecholamine sympathomimetic amines with CNS stimulant activity. The mode of therapeutic action in Attention Deficit Hyperactivity Disorder (ADHD) is not known. Amphetamines are thought to block the reuptake of norepinephrine and dopamine into the presynaptic neuron and increase the release of these monoamines into the extraneuronal space.

Pharmacokinetics

Tablets of Mixed Salts of a Single Entity Amphetamine Product contain d-amphetamine and I-amphetamine salts in the ration of 3:1. Following administration of a single dose 10 or 30 mg of Tablets of Mixed Salts of a Single Entity Amphetamine Product to healthy volunteers under fasted conditions, peak plasma concentrations occurred approximately 3 hours post-dose for both d-amphetamine and I-amphetamine. The mean elimination half-life (t½) for d-amphetamine was shorter than the t½ of the l-isomer (9.77 to 11 hours vs. 11.5 to 13.8 hours). The PK parameters (Cmax, AUC0-inf) of d-and l-amphetamine increased approximately three-fold from 10 mg to 30 mg indicating dose-proportional pharmacokinetics.

The effect of food on the bioavailability of Tablets of Mixed Salts of a Single Entity Amphetamine Product has not been studied.

Metabolism and Excretion

Amphetamine is reported to be oxidized at the 4 position of the benzene ring to form 4-hydroxyamphetamine, or on the side chain α or β carbons to form alpha-hydroxy-amphetamine or norephedrine, respectively. Norephedrine and 4-hydroxy-amphetamine are both active and each is subsequently oxidized to form 4-hydroxy-norephedrine. Alpha-hydroxy-amphetamine undergoes deamination to form phenylacetone, which ultimately forms benzoic acid and its glucuronide and the glycine conjugate hippuric acid. Although the enzymes involved in amphetamine metabolism have not been clearly defined, CYP2D6 is known to be involved with formation of 4-hydroxy-amphetamine. Since CYP2D6 is genetically polymorphic, population variations in amphetamine metabolism are a possibility.

Amphetamine is known to inhibit monoamine oxidase, whereas the ability of amphetamine and its metabolites to inhibit various P450 isozymes and other enzymes has not been adequately elucidated. In vitro experiments with human microsomes indicate minor inhibition of CYP2D6 by amphetamine and minor inhibition of CYP1A2, 2D6, and 3A4 by one or more metabolites. However, due to the probability of auto-inhibition and the lack of information on the concentration of these metabolites relative to in vivo concentrations, no predications regarding the potential for amphetamine or its metabolites to inhibit the metabolism of other drugs by CYP isozymes in vivo can be made.

With normal urine pHs approximately half of an administered dose of amphetamine is recoverable in urine as derivatives of alpha-hydroxy-amphetamine and approximately another 30% to 40% of the dose is recoverable in urine as amphetamine itself. Since amphetamine has a pKa of 9.9, urinary recovery of amphetamine is highly dependent on pH and urine flow rates. Alkaline urine pHs result in less ionization and reduced renal elimination, and acidic pHs and high flow rates result in increased renal elimination with clearances greater than glomerular filtration rates, indicating the involvement of active secretion. Urinary recovery of amphetamine has been reported to range from 1% to 75%, depending on urinary pH, with the remaining fraction of the dose hepatically metabolized. Consequently, both hepatic and renal dysfunction have the potential to inhibit the elimination of amphetamine and result in prolonged exposures. In addition, drugs that effect urinary pH are known to alter the elimination of amphetamine, and any decrease in amphetamine's metabolism that might occur due to drug interactions or genetic polymorphisms is more likely to be clinically significant when renal elimination is decreased, (see PRECAUTIONS).

INDICATIONS AND USAGE

Tablets of Mixed Salts of a Single Entity Amphetamine product are indicated for the treatment of Attention Deficit Hyperactivity Disorder (ADHD) and Narcolepsy.

Attention Deficit Hyperactivity Disorder (ADHD)

A diagnosis of Attention Deficit Hyperactivity Disorder (ADHD; DSM-IV®) implies the presence of hyperactive-impulsive or inattentive symptoms that caused impairment and were present before age 7 years. The symptoms must cause clinically significant impairment, e.g., in social, academic, or occupational functioning, and be present in two or more settings, e.g., school (or work) and at home. The symptoms must not be better accounted for by another mental disorder. For the Inattentive Type, at least six of the following symptoms must have persisted for at least 6 months: lack of attention to details/careless mistakes; lack of sustained attention; poor listener; failure to follow through on tasks; poor organization; avoids tasks requiring sustained mental effort; loses things; easily distracted; forgetful. For the Hyperactive-Impulsive Type, at least six of the following symptoms must have persisted for at least 6 months: fidgeting/squirming; leaving seat; inappropriate running/climbing; difficulty with quiet activities; “on the go;” excessive talking; blurting answers; can't wait turn; intrusive. The Combined Type requires both inattentive and hyperactive-impulsive criteria to be met.

Special Diagnostic Considerations- Specific etiology of this syndrome is unknown, and there is no single diagnostic test. Adequate diagnosis requires the use not only of medical but of special psychological, educational, and social resources. Learning may or may not be impaired. The diagnosis must be based upon a complete history and evaluation of the child and not solely on the presence of the required number of DSM-IV® characterostocs/

Need for Comprehensive Treatment Program- Tablets of Mixed Salts of a Single Entity Amphetamine Product are indicated as an integral part of a total treatment program for ADHD that may include other measures (psychological, educational, social) for patients with this syndrome. Drug treatment may not be indicated for all children with this syndrome. Stimulants are not intended for use in the child who exhibits symptoms secondary to environmental factors and/or other primary psychiatric disorders, including psychosis. Appropriate educational placement is essential and psychosocial intervention is often helpful. When remedial measures alone are insufficient, the decision to prescribe stimulant medication will depend upon the physician's assessment of the chronicity and severity of the child's symptoms.

Long-Term Use- The effectiveness of Tablets of Mixed Salts of a Single Entity Amphetamine Product for long-term use has not been systematically evaluated in controlled trials. Therefore, the physician who elects to use Tablets of Mixed Salts of a Single Entity Amphetamine Product for extended periods should periodically re-evaluate the long-term usefulness of the drug for the individual patient.

CONTRAINDICATIONS

Advanced arteriosclerosis, symptomatic cardiovascular disease, moderate to severe hypertension, hyperthyroidism, known hypersensitivity or idiosyncrasy to the sympathomimetic amines, glaucoma.

Agitated states.

Patients with a history of drug abuse.

During or within 14 days following the administration of monoamine oxidase inhibitors (hypertensive crises may result).

WARNINGS

Serious Cardiovascular Events

Sudden Death and Pre-existing Structural Cardiac Abnormalities or Other Serious Heart Problems

Children and Adolescents– Sudden death has been reported in association with CNS stimulant treatment at usual doses in children and adolescents with structural cardiac abnormalities or other serious heart problems. Although some structural heart problems alone may carry an increased risk of sudden death, stimulant products generally should not be used in children or adolescents with known structural cardiac abnormalities, cardiomyopathy, serious heart rhythm abnormalities, or other serious cardiac problems that may place them at increased vulnerability to the sympathomimetic effects of a stimulant drug (see CONTRAINDICATIONS).

Adults– Sudden deaths, stroke, and myocardial infarction have been reported in adults taking stimulant drugs at usual doses for ADHD. Although the role of stimulants in these adult cases is also unknown, adults have a greater likelihood than children of having serious structural cardiac abnormalities, cardiomyopathy, serious heart rhythm abnormalities, coronary artery disease, or other serious cardiac problems. Adults with such abnormalities should also generally not be treated with stimulant drugs (see CONTRAINDICATIONS).

Hypertension and Other Cardiovascular Conditions

Stimulant medications cause a modes increase in average blood pressure 9about 2 to 4 mmHg) and average heart rate (about 3 to 6 bpm) [see ADVERSE REACTIONS], and individuals may have larger increases. While the mean changes alone would not be expected to have short-term consequences, all patients should be monitored for larger changes in heart rate and blood pressure. Caution is indicated in treating patients whose underlying medical conditions might be compromised by increases in blood pressure or heart rate, e.g., those with pre-existing hypertension, heart failure, recent myocardial infarction, or ventricular arrhythmia (see CONTRAINDICATIONS). Assessing Cardiovascular Status in Patients being Treated with Stimulant Medications.

Children, adolescents, or adults who are being considered for treatment with stimulant medications should have a careful history (including assessment for a family history of sudden death or ventricular arrhythmia) and physical exam to assess for the presence of cardiac disease, and should receive further cardiac evaluation if findings suggest such disease (e.g. electrocardiogram and echocardiogram). Patients who develop symptoms such as exertional chest pain, unexplained syncope, or other symptoms suggestive of cardiac disease during stimulant treatment should undergo a prompt cardiac evaluation.

Psychiatric Adverse Events

Pre-Existing Psychosis- Admiistration of stimulants may exacerbate symptoms of behavior disturbance and thought disorder in patients with pre-existing psychotic disorder.

Bipolar Illness- Particular care should be taken i using stimulants to treat ADHD patients with comorbid comorbid bipolar disorder because of concern for possible induction of mixed/manic episode in such patients. Prior to initiating treatment with a stimulant, patients with comorbid depressive symptoms should be adequately screened to determine if they are at risk for bipolar disorder; such screening should include a detailed psychiatric history, including a family history of suicide, bipolar disorder, and depression.

Emergence of New Psychotic or Manic Symptoms- Treatment emergent psychotic or manic symptoms, e.g., hallucinations, delusional thinking, or mania in children and adolescents without prior history of psychotic illness or mania can be caused by stimulants at usual doses. If such symptoms occur, consideration should be given to a possible causal role of the stimulant, and discontinuation of treatment may be appropriate. In a pooled analysis of multiple short-term, placebo-controlled studies, such symptoms occurred in about 0.1% (4 patients with events out of 3482 exposed to methylphenidate or amphetamine for several weeks at usual doses) of stimulant-treated patients compared to 0 in placebo-treated patients.

Aggression- Aggressive behavior or hostility is often observed in children and adolescents with ADHD, and has been reported in clinical trials and the postmarketing experience of some medications indicated for the treatment of ADHD. Although there is no systematic evidence that stimulants cause aggressive behavior or hostility, patients beginning treatment for ADHD should be monitored for the appearance of or worsening of aggressive behavior or hostility.

Long-term Suppression of Growth

Careful follow-up of weight and height in children ages 7 to 10 years who were randomized to either methylphenidate or non-medication treatment groups over 14 months, as well as in naturalistic subgroups of newly methylphenidate-treated and non-medication treated children over 36 months (to the ages of 10 to 13 years), suggests that consistently medicated children (i.e., treatment for 7 days per week throughout the year) have a temporary slowing in growth rate (on average, a total of about 2 cm less growth in height and 2.7 kg less growth in weight over 3 years), without evidence of growth rebound during this period of development. Published data are inadequate to determine whether chronic use of amphetamines may cause a similar suppression of growth, however, it is anticipated that they will likely have this effect as well. Therefore, growth should be monitored during treatment with stimulants, and patients who are not growing or gaining weight as expected may need to have their treatment interrupted.

Seizures

There is some clinical evidence that stimulants may lower the convulsive threshold in patients with prior history of seizure, in patients with prior EEG abnormalities in absence of seizures, and very rarely, in patients without a history of seizures and no prior EEG evidence of seizures. In the presence of seizures, the drug should be discontinued.

Visual Disturbance

Difficulties with accommodation and blurring of vision have been reported with stimulant treatment.

PRECAUTIONS

General

The least amount of amphetamine feasible should be prescribed or dispensed at one time in order to minimize the possibility of overdosage. Tablets of Mixed Salts of a Single Entity Amphetamine Product should be used with caution in patients who use other sympathomimetic drugs.

Tics

Amphetamines have been reported to exacerbate motor and phonic tics and Tourette's syndrome. Therefore, clinical evaluation for tics and Tourette's syndrome in children and their families should precede use of stimulant medications.

Information for Patients

Amphetamines may impair the ability of the patient to engage in potentially hazardous activities such as operating machiner or vehicles; the patient should therefore be cautioned accordingly.

Drug Interactions

Acidifying agents - Gastrointestinal acidifying agents (guadethidine, reserpine, glutamic acid HCI, ascorbic acid fruit juices, etc.) lower absorption of amphetamines.

Urinary acidifying agents - (ammonium chloride, sodium acid phosphate, etc.) Increase the concentration of the ionized species of the amphetamine molecule, thereby increasing urinary excretion. Both groups of agents lower blood levels and efficacy of amphetamines.

Adrenergic blocker - Adrenergic blockers are inhibited by amphetamines.

Alkalinizing agents - Gastrointestinal alkalinizing agents (sodium bicarbonate, etc.) increase absorption of amphetamines. Co-administration of Tablets of Mixed Salts of a Single Entity Amphetamine Product and gastrointestinal alkalizing agents, such as antacids, should be avoided. Urinary alkalinizing agents (acetazolamide, some thiazides) increase the concentration of the non-ionized species of the amphetamine molecule, thereby decreasing urinary excretion. Both groups of agents increase blood levels and therefore potentiate the actions of amphetamines.

Antidepressants, tricyclic - Amphetamines may enhance the activity of tricyclic or sympathomimetic agents; d-amphetamine with desipramine or protriptyline and possibly other tricyclics cause striking and sustained increases in the concentration of d-amphetamine in the brain; cardiovascular effects can be potentiated.

MAO inhibitors - MAOI antidepressants, as well as a metabolite of furazolidone, slow amphetamine metabolism. This slowing potentiates amphetamines, increasing their effect on the release of norepinephrine and other monoamines from adrenergic nerve endings; this can cause headaches and other signs of hypertensive crisis. A variety of neurological toxic effects and malignant hyperpyrexia can occur, sometimes with fatal results.

Antihistamines - Amphetamines may counteract the sedative effect of antihistamines.

Antihypertensives - Amphetamines may antagonize the hypotensive effects of antihypertensives.

Chlorpromazine - Chlorpromazine blocks dopamine and norepinephrine receptors, thus inhibiting the central stimulants effects of amphetamines, and can be used to treat amphetamine poisoning.

Ethosuximide - Amphetamines may delay intestinal absorption of ethosuximide.

Haloperidol - Haloperidol blocks dopamine receptors, thus inhibiting the central stimulant effects of amphetamines.

Lithium carbonate - The anorectic and stimulatory effects of amphetamines may be inhibited by lithium carbonate.

Meperidine - Amphetamines potentiate the analgesic effect of meperidine.

Methenamine therapy - Urinary excretion of amphetamines is increased, and efficacy is reduced, by acidifying agents used in methenamine therapy.

Norepinephrine - Amphetamines enhance the adrenergic effect of norepinephrine.

Phenytoin - Amphetaimes may delay intestinal absorption of phenytoin; co-administration of phenytoin may produce a synergistic anticonvulsant action.

Propoxyphene - In cases of propoxyphene overdosage, amphetamine CNS stimulation is potentiated and fatal convulsions can occur.

Veratrum alkaloids - Amphetamines inhibit the hypotensive effect of veratrum alkaloids.

Drug/Laboratory Test Interactions

Amphetamines can cause a significant elevation in plasma corticosteroid levels. This increase is greatest in the evening.

Amphetamines may interfere with urinary steroid determinations.

Carcinogenesis/Mutagenesis and Impairment of Fertility

No evidence of carcinogenicity was found in studies in which d, I-amphetamine (enantiomer ration of 1:1) was administered to mice and rats in the diet for 2 years at doses of up to 30 mg/kg/day in male mice, 19 mg/kg/day in female mice, and 5 mg/kg/day in male and female rats. These doses are approximately 2.4, 1.5, and 0.8 times, respectively, the maximum recommended human dose of 30 mg/day [child] on a mg/m^2 body surface area basis.

Amphetamine, in the enantiomer ratio present in Tablets of Mixed Salts of a Single Entity Amphetamine product (immediate-release)(d- to I- ratio of 3:1), was not clastogenic in the mouse bone marrow micronucleus test in vivo and was negative when tested in the E. coli component of the Ames test in vitro. d, I-Amphetamine (1:1 enantiomer ratio) has been reported to produce a positive response in the mouse bone marrow micronucleus test, an equivocal response in the Ames test, and negative responses in the in vitro sister chromatid exchange and chromosomal aberration assays.

Amphetamine, in the enantiomer ratio present in Tablets of Mixed Salts of a Single Entity Amphetamine product (immediate-release)(d- to I- ratio of 3:1), did not adversely affect fertility or early embryonic development in the rat at doses of up to 20 mg/kg/day (approximately 5 times the maximum recommended human dose of 30 mg/day on a mg/m^2 body surface area basis).

Pregnancy

Teratogenic Effects. Pregnancy Category C - Amphetamine, in the enantiomer ratio present in Tablets of mixed Salts of a Single Entity Amphetamine product (d- to I- ratio of 3:1), had no apparent effects on embryofetal morphological development or survival when orally administered to pregnant rats and rabbits throughout the period of organogenesis at doses of up to 6 and 16 mg/kg/day, respectively. These doses are approximately 1.5 and 8 times, respectively, the maximum recommended human dose of 30 mg/day [child] on a mg/m^2 body surface area basis. Fetal malformations and death have been reported in mice following parenteral administration of d-amphetamine doses of 50 mg/kg/day (approximately 6 times that of a human dose of 30 mg/day [child] on a mg/m^2 basis) or greater to pregnant animals. Administration of these doses was also associated with severe maternal toxicity.

A number of studies in rodents indicate that prenatal or early postnatal exposure to amphetamine (d- or d,I-), at doses similar to those used clinically, can result in long-term neurochemical and behavioral alterations. Reported behavioral effects include learning and memory deficits, altered locomotor activity, and changes in sexual function.

There are no adequate and well-controlled studies in pregnant women. There has been one report of severe congenital bony deformity, tracheo-esophageal fistula, and anal atresia (vater association) in a baby born to a woman who took dextroamphetamine sulfate with lovastatin during the first trimester of pregnancy. Amphetamines should be used during pregnancy only if the potential benefit justifies the potential risk to the fetus.

Nonteratogenic Effects - Infants born to mothers dependent on amphetamines have an increased risk of premature delivery and low birth weight. Also, these infants may experience symptoms of withdrawal as demonstrated by dysphoria, including agitation, and significant lassitude.

Usage in Nursing Mothers - Amphetamines are excreted in human milk. Mothers taking amphetamines should be advised to refrain from nursing.

Pediatric Use - Long-term effects of amphetamines in children have not been well established. Amphetamines are not recommended for use in children under 3 years of age with Attention Deficit Hyperactivity Disorder described under INDICATIONS AND USAGE.

Geriatric Use - Tablets of Mixed Salts of a Single Entity Amphetamine Product have not been studied in the geriatric population.

ADVERSE REACTIONS

Cardiovascular– Palpitations, tachycardia, elevation of blood pressure, sudden death, myocardial infarction. There have been isolated reports of cardiomyopathy associated with chronic amphetamine use.

Central Nervous System– Psychotic episodes at recommended doses, overstimulation, restlessness, dizziness, insomnia, euphoria, dyskinesia, dysphoria, depression, tremor, headache, exacerbation of motor and phonic tics and Tourette's syndrome, seizures, stroke.

Gastrointestinal– Dryness of the mouth, unpleasant taste, diarrhea, constipation, other gastrointestinal disturbances. Anorexia and weight loss may occur as undesirable effects.

Allergic– Urticaria, rash, hypersensitivity reactions including angioedema and anaphylaxis. Serious skin rashes, including Stevens Johnson Syndrome and toxic epidermal necrolysis have been reported.

Endocrine– Impotence, changes in libido.

DRUG ABUSE AND DEPENDENCE

Dextroamphetamine sulfate is a Schedule II controlled substance.

Amphetamines have been extensively abused. Tolerance, extreme psychological dependence, and severe social disability have occurred. There are reports of patients who have increased the dosage to levels many times higher than recommended. Abrupt cessation following prolonged high dosage administration results in extreme fatigue and mental depression; changes are also noted on the sleep EEG. Manifestations of chronic intoxication with amphetamines include severe dermatoses, marked insomnia, irritability, hyperactivity, and personality changes

OVERDOSAGE

Individual patient response to amphetamines varies widely. Toxic symptoms may occur idiosyncratically at low doses.

Symptoms

Manifestations of acute overdosage with amphetamines include restlessness, tremor, hyperreflexia, rapid respiration, confusion, assaultiveness, hallucinations, panic states, hyperpyrexia and rhabdomyolysis.

Fatigue and depression usually follow the central stimulation.

Cardiovascular effects include arrhythmias, hypertension or hypotension and circulatory collapse.

GASTROINTESTINAL SYMPTOMS INCLUDE NAUSEA, VOMITING DIARRHEA, AND ABDOMINAL CRAMPS. FATAL POISONING IS USUALLY PRECEDED BY CONVULSIONS AND COMA.

Treatment

CONSULT WITH A CERTIFIED POISON CONTROL CENTER FOR UP TO DATE GUIDANCE AND ADVISE. MANAGEMENT OF ACUTE AMPHETAMINE INTOXICATION IS LARGELY SYMPTOMATIC AND INCLUDES GASTRIC LAVAGE, ADMINISTRATION OF ACTIVATED CHARCOAL, ADMINISTRATION OF A CATHARTIC AND SEDATION. EXPERIENCE WITH HEMODIALYSIS OR PERITONEAL DIALYSIS IS INADEQUATE TO PERMIT RECOMMENDATION IN THIS REGARD. ACIDIFICATION OF THE URINE INCREASES AMPHETAMINE EXCRETION, BUT IS BELIEVED TO INCREASE RISK OF ACUTE RENAL FAILURE IF MYOGLOBINURIA IS PRESENT. IF ACUTE, SEVERE HYPERTENSION COMPLICATES AMPHETAMINE OVERDOSAGE, ADMINISTRATION OF INTRAVENOUS PHENTOLAMINE (REGITINE®, CIBA) HAS BEEN SUGGESTED. HOWEVER, A GRADUAL DROP IN BLOOD PRESSURE WILL USUALLY RESULT WHEN SUFFICIENT SEDATION HAS BEEN ACHIEVED. CHLORPROMAZINE ANTAGONIZES THE CENTRAL STIMULANT EFFECTS OF AMPHETAMINES AND CAN BE USED TO TREAT AMPHETAMINE INTOXICATION.

DOSAGE AND ADMINISTRATION

Regardless of indication, amphetamines should be administered at the lowest effective dosage and dosage should be individually adjusted to the therapeutic needs and response of the patient. Late evening doses should be avoided because of the resulting insomnia.

Attention Deficit Hyperactivity Disorder

Not recommended for children under 3 years of age. In children from 3 to 5 years of age, start with 2.5 mg daily; daily dosage may be raised in increments of 2.5 mg at weekly intervals until optimal response is obtained.

In children 6 years of age and older, start with 5 mg once or twice daily; daily dosage may be raised in increments of 5 mg at weekly intervals until optimal response is obtained. Only in rare cases will it be necessary to exceed a total of 40 mg per day. Give first dose on awakening; additional doses (1 or 2) at intervals of 4 to 6 hours.

Where possible, drug administration should be interrupted occasionally to determine if there is a recurrence of behavioral symptoms sufficient to require continued therapy.

Narcolepsy

Usual dose 5 mg to 60 mg per day in divided doses, depending ion the individual patient response.

Narcolepsy seldom occurs in children under 12 years of age; however, when it does, dextroamphetamine sulfate may be used. The suggested initial dose for patients aged 6 to 12 is 5 mg daily; daily dose may be raised in increments of 5 mg at weekly intervals until optimal response is obtained. In patients 12 years of age and older, start with 10 mg daily; daily dosage may be raised in increments of 10 mg at weekly intervals until optimal response is obtained. If bothersome adverse reactions appear (e.g., insomnia or anorexia), dosage should be reduced. Give first dose on awakening; additional doses (1 or 2) at intervals of 4 to 6 hours.

HOW SUPPLIED

Dextroamphetamine Saccharate, Amphetamine Aspartate, Dextroamphetamine Sulfate, Amphetamine Sulfate Tablets (Mixed Salts of a Single Entity Amphetamine Product) are supplied as follows:

5 mg: | White to cream colored pillow shaped tablet, debossed with a “5” and a partial quadrisect on one side and a on the other side. Bottles of 20 NDC 54868-4631-1 Bottles of 30 NDC 54868-4631-2 Bottles of 60 NDC 54868-4631-3 Bottles of 100 NDC 54868-4631-0
10 mg: | White to cream colored pillow shaped tablet, debossed with a “10” and a partial quadrisect on one side and a on the other side. Bottles of 10 NDC 54868-4728-0 Bottles of 30 NDC 54868-4728-1 Bottles of 60 NDC 54868-4728-2 Bottles of 90 NDC 54868-4728-3 Bottles of 100 NDC 54868-4728-4 Bottles of 120 NDC 54868-4728-5
15 mg: | White to cream colored octagon shaped tablet, debossed with a “15” and a partial quadrisect on one side and a on the other side. Bottles of 30 NDC 54868-5387-1 Bottles of 90 NDC 54868-5387-0
20 mg: | White to cream colored octagon shaped tablet, debossed with a “20” and a partial quadrisect on one side and a on the other side. Bottles of 10 NDC 54868-5103-4 Bottles of 20 NDC 54868-5103-3 Bottles of 30 NDC 54868-5103-0 Bottles of 60 NDC 54868-5103-1 Bottles of 90 NDC 54868-5103-2 Bottles of 100 NDC 54868-5103-6 Bottles of 120 NDC 54868-5103-5
30 mg: | White to cream colored octagon shaped tablet, debossed with a “30” and a partial quadrisect on one side and a on the other side. Bottles of 10 NDC 54868-4863-1 Bottles of 30 NDC 54868-4863-0 Bottles of 60 NDC 54868-4863-2 Bottles of 90 NDC 54868-4863-3

Dispense in a tight, light-resistant container with a child-resistant closure.

Store at 20° to 25°C (68° to 77°F) [see USP Controlled Room Temperature].

is a registered trademark of Mallinckrodt Inc.

tyco
Healthcare
Mallinckrodt

Mallinckrodt Inc.
St. Louis, MO 63134 U.S.A.

Printed in U.S.A.
Rev 092006

Repackaging and Relabeling by:
Physicians Total Care, Inc.
Tulsa, OK 74146

PRINCIPAL DISPLAY PANEL

Dextroamphetamine Saccharate, Amphetamine Aspartate, Dextroamphetamine Sulfate, Amphetamine Sulfate Tablets (Mixed Salts of a Single Entity Amphetamine Product)

5 mg:

10 mg:

15 mg:

20 mg:

30 mg:

MEDICATION GUIDE

DEXTROAMPHETAMINE SACCHARATE, AMPHETAMINE ASPARTATE, DEXTROAMPHETAMINE SULFATE, and AMPHETAMINE SULFATE TABLETS CII

Read the Medication Guide that comes with dextroamphetamine saccharate, amphetamine aspartate, dextroamphetamine sulfate, and amphetamine sulfate tablets before you or your child starts taking it and each time you get a refill. There may be new information. This Medication Guide does not take the place of talking to your doctor about you or your child's treatment with dextroamphetamine saccharate, amphetamine aspartate, dextroamphetamine sulfate, and amphetamine sulfate tablets.

What is the most important information I should know about dextroamphetamine saccharate, amphetamine aspartate, dextroamphetamine sulfate, and amphetamine sulfate tablets?

The following have been reported with use of dextroamphetamine saccharate, amphetamine aspartate, dextroamphetamine sulfate, and amphetamine sulfate and other stimulant medicines.

1.Heart-related problems:

- sudden death in patients who have heart problems or heart defects
- stroke and heart attack in adults
- increased blood pressure and heart rate

Tell your doctor if you or your child have any heart problems, heart defects, high blood pressure, or a family history of these problems.

Your doctor should check you or your child carefully for heart problems before starting dextroamphetamine saccharate, amphetamine aspartate, dextroamphetamine sulfate, and amphetamine sulfate.

Your doctor should check you or your child's blood pressure and heart rate regularly during treatment with dextroamphetamine saccharate, amphetamine aspartate, dextroamphetamine sulfate, and amphetamine sulfate.

Call your doctor right away if you or your child has any signs of heart problems such as chest pain, shortness of breath, or fainting while taking dextroamphetamine saccharate, amphetamine aspartate, dextroamphetamine sulfate, and amphetamine sulfate.

2.Mental (Psychiatric) problems:

All Patients

- new or worse behavior and thought problems
- new or worse bipolar illness
- new or worse aggressive behavior or hostility

Children and Teenagers

- new psychotic symptoms (such as hearing voices, believing things that are not true, are suspicious) or new manic symptoms

Tell your doctor about any mental problems you or your child have, or about a family history of suicide, bipolar illness, or depression.

Call your doctor right away if you or your child have any new or worsening mental symptoms or problems while taking dextroamphetamine saccharate, amphetamine aspartate, dextroamphetamine sulfate, and amphetamine sulfate, especially seeing or hearing things that are not real, believing things that are not real, or are suspicious.

What is dextroamphetamine saccharate, amphetamine aspartate, dextroamphetamine sulfate, and amphetamine sulfate?

Dextroamphetamine saccharate, amphetamine aspartate, dextroamphetamine sulfate, and amphetamine sulfate is a central nervous system stimulant prescription medicine.

It is used for the treatment of Attention Deficit Hyperactivity Disorder (ADHD). Dextroamphetamine saccharate, amphetamine aspartate, dextroamphetamine sulfate, and amphetamine sulfate may help increase attention and decrease impulsiveness and hyperactivity in patients with ADHD.

Dextroamphetamine saccharate, amphetamine aspartate, dextroamphetamine sulfate, and amphetamine sulfate should be used as a part of a total treatment program for ADHD that may include counseling or other therapies.

Dextroamphetamine saccharate, amphetamine aspartate, dextroamphetamine sulfate, and amphetamine sulfate is also used in the treatment of a sleep disorder called narcolepsy.

Dextroamphetamine saccharate, amphetamine aspartate, dextroamphetamine sulfate, and amphetamine sulfate tablets is a federally controlled substance (CII) because it can be abused or lead to dependence. Keep dextroamphetamine saccharate, amphetamine aspartate, dextroamphetamine sulfate, and amphetamine sulfate tablets in a safe place to prevent misuse and abuse. Selling or giving away dextroamphetamine saccharate, amphetamine aspartate, dextroamphetamine sulfate, and amphetamine sulfate tablets may harm others, and is against the law.

Tell your doctor if you or your child have (or have a family history of) ever abused or been dependent on alcohol, prescriptions medicines or street drugs.

Who should not take dextroamphetamine saccharate, amphetamine aspartate, dextroamphetamine sulfate, and amphetamine sulfate tablets?

Dextroamphetamine saccharate, amphetamine aspartate, dextroamphetamine sulfate, and amphetamine sulfate tablets should not be taken if you or your child:

- have heart disease or hardening of the arteries
- have moderate to severe high blood pressure
- have hyperthyroidism
- have an eye problem called glaucoma
- are very anxious, tense, or agitated
- have a history of drug abuse
- are taking or have taken within the past 14 days an anti-depression medicine called a monoamine oxidase inhibitor or MAOI.
- is sensitive to, allergic to, or had a reaction to other stimulant medicines

Dextroamphetamine saccharate, amphetamine aspartate, dextroamphetamine sulfate, and amphetamine sulfate tablets are not recommended for use in children less than 3 years old.

Dextroamphetamine saccharate, amphetamine aspartate, dextroamphetamine sulfate, and amphetamine sulfate may not be right for you or your child. Before starting dextroamphetamine saccharate, amphetamine aspartate, dextroamphetamine sulfate, and amphetamine sulfate tell your or your child's doctor about all health conditions (or a family history of) including:

- heart problems, heart defects, high blood pressure
- mental problems including psychosis, mania, bipolar illness, or depression
- tics or Tourette's syndrome
- liver or kidney problems
- thyroid problems
- seizures or have had an abnormal brain wave test (EEG)

Tell your doctor if you or your child is pregnant, planning to become pregnant, or breastfeeding.

Can dextroamphetamine saccharate, amphetamine aspartate, dextroamphetamine sulfate, and amphetamine sulfate tablets be taken with other medicines?

Tell your doctor about all of the medicines that you or your child take including prescription and nonprescription medicines, vitamins, and herbal supplements.

Dextroamphetamine saccharate, amphetamine aspartate, dextroamphetamine sulfate, and amphetamine sulfate and some medicines may interact with each other and cause serious side effects. Sometimes the doses of other medicines will need to be adjusted while taking dextroamphetamine saccharate, amphetamine aspartate, dextroamphetamine sulfate, and amphetamine sulfate tablets.

Your doctor will decide whether dextroamphetamine saccharate, amphetamine aspartate, dextroamphetamine sulfate, and amphetamine sulfate tablets can be taken with other medicines.

Especially tell your doctor if you or your child takes:

- anti-depression medicines including MAOIs
- seizure medicines
- blood thinner medicines
- blood pressure medicines
- stomach acid medicines
- cold or allergy medicines that contain decongestants

Know the medicines that you or your child takes. Keep a list of your medicines with you to show your doctor and pharmacist.

Do not start any new medicine while taking dextroamphetamine saccharate, amphetamine aspartate, dextroamphetamine sulfate, and amphetamine sulfate without talking to your doctor first.

How should dextroamphetamine saccharate, amphetamine aspartate, dextroamphetamine sulfate, and amphetamine sulfate be taken?

- Take dextroamphetamine saccharate, amphetamine aspartate, dextroamphetamine sulfate, and amphetamine sulfate exactly as prescribed. Your doctor may adjust the dose until it is right for you or your child.
- Dextroamphetamine saccharate, amphetamine aspartate, dextroamphetamine sulfate, and amphetamine sulfate tablets are usually taken two to three times a day. The first dose is usually taken when you first wake in the morning. One or two more doses may be taken during the day, 4 to 6 hours apart.
- Dextroamphetamine saccharate, amphetamine aspartate, dextroamphetamine sulfate, and amphetamine sulfate tablets can be taken with or without food.
- From time to time, your doctor may stop dextroamphetamine saccharate, amphetamine aspartate, dextroamphetamine sulfate, and amphetamine sulfate treatment for a while to check ADHD symptoms.
- Your doctor may do regular checks of the blood, heart, and blood pressure while taking dextroamphetamine saccharate, amphetamine aspartate, dextroamphetamine sulfate, and amphetamine sulfate. Children should have their height and weight checked often while taking dextroamphetamine saccharate, amphetamine aspartate, dextroamphetamine sulfate, and amphetamine sulfate. Dextroamphetamine saccharate, amphetamine aspartate, dextroamphetamine sulfate and amphetamine sulfate treatment may be stopped if a problem is found during these check-ups.
- If you or your child takes too much dextroamphetamine saccharate, amphetamine aspartate, dextroamphetamine sulfate, and amphetamine sulfate or overdoses, call your doctor or poison control center right away, or get emergency treatment.

What are possible side effects of dextroamphetamine saccharate, amphetamine aspartate, dextroamphetamine sulfate, and amphetamine sulfate?

See "What is the most important information I should know about dextroamphetamine saccharate, amphetamine aspartate, dextroamphetamine sulfate, and amphetamine sulfate?" for information on reported heart and mental problems.

Other serious side effects include:

- slowing of growth (height and weight) in children
- seizures, mainly in patients with a history of seizures
- eyesight changes or blurred vision

Common side effects include:

- headache
- stomach ache
- trouble sleeping
- decreased appetite
- nervousness
- dizziness

Dextroamphetamine saccharate, amphetamine aspartate, dextroamphetamine sulfate, and amphetamine sulfate may affect you or your child's ability to drive or do other dangerous activities.

Talk to your doctor if you or your child has side effects that are bothersome or do not go away.

This is not a complete list of possible side effects. Ask your doctor or pharmacist for more information

How should I store dextroamphetamine saccharate, amphetamine aspartate, dextroamphetamine sulfate, and amphetamine sulfate tablets?

- Store dextroamphetamine saccharate, amphetamine aspartate, dextroamphetamine sulfate, and amphetamine sulfate in a safe place at room temperature, 20° to 25°C (68° to 77°F).
- Keep dextroamphetamine saccharate, amphetamine aspartate, dextroamphetamine sulfate, and amphetamine sulfate and all medicines out of the reach of children.

General information about dextroamphetamine saccharate, amphetamine aspartate, dextroamphetamine sulfate, and amphetamine sulfate

Medicines are sometimes prescribed for purposes other than those listed in a Medication Guide. Do not use dextroamphetamine saccharate, amphetamine aspartate, dextroamphetamine sulfate, and amphetamine sulfate for a condition for which it was not prescribed. Do not give dextroamphetamine saccharate, amphetamine aspartate, dextroamphetamine sulfate, and amphetamine sulfate to other people, even if they have the same condition. It may harm them and it is against the law.

This Medication Guide summarizes the most important information about dextroamphetamine saccharate, amphetamine aspartate, dextroamphetamine sulfate, and amphetamine sulfate. If you would like more information, talk with your doctor. You can ask your doctor or pharmacist for information about dextroamphetamine saccharate, amphetamine aspartate, dextroamphetamine sulfate, and amphetamine sulfate that was written for healthcare professionals. For more information, you may also contact Mallinckrodt Inc.., (the maker of dextroamphetamine saccharate, amphetamine aspartate, dextroamphetamine sulfate, and amphetamine sulfate tablets) at 1-800-325-8888.

What are the ingredients in dextroamphetamine saccharate, amphetamine aspartate, dextroamphetamine sulfate, and amphetamine sulfate tablets?

Active Ingredients: dextroamphetamine saccharate, amphetamine aspartate monohydrate, dextroamphetamine sulfate, amphetamine sulfate

Inactive Ingredients: Microcrystalline Cellulose NF, Silicon Dioxide NF, Povidone USP, and Stearic Acid NF.

This Medication Guide has been approved by the U.S. Food and Drug Administration.